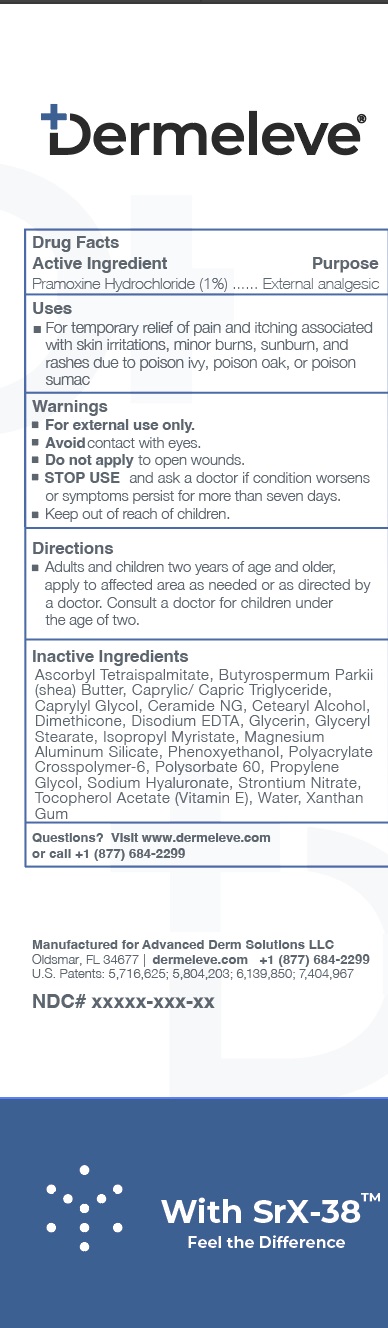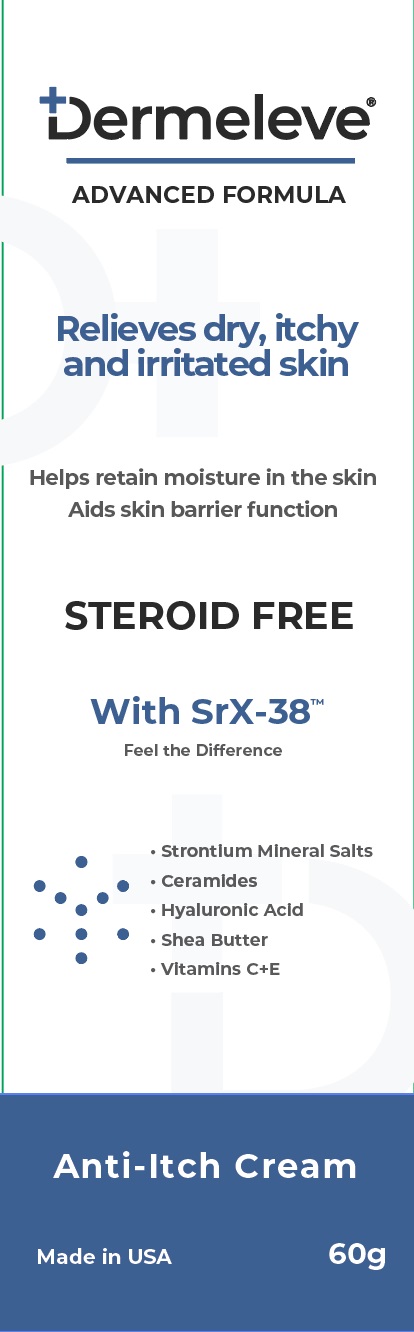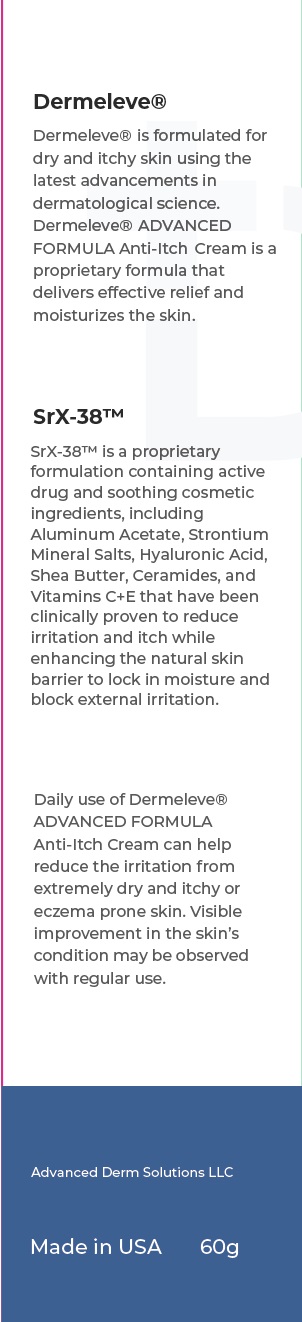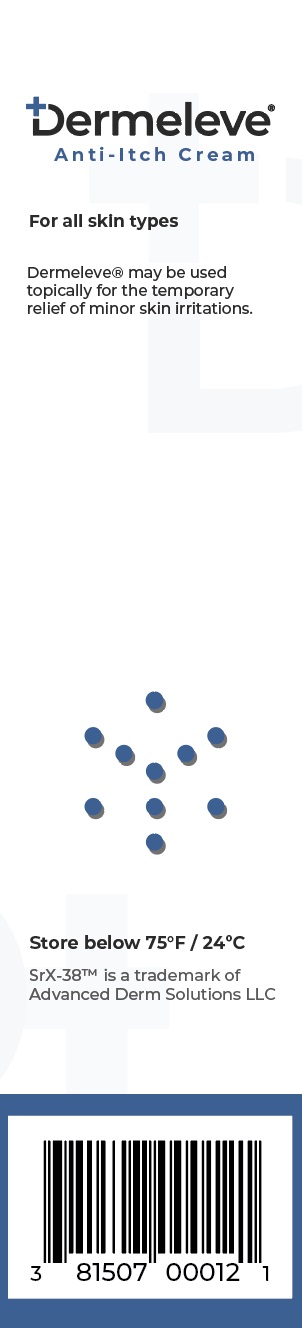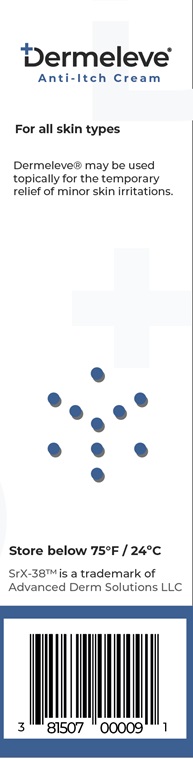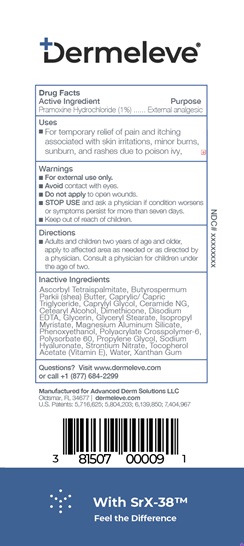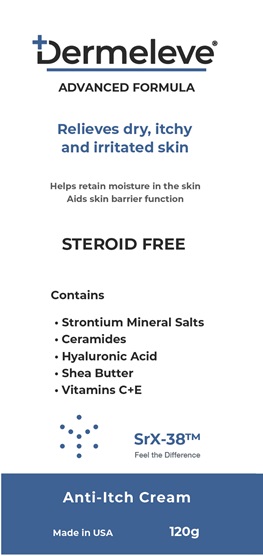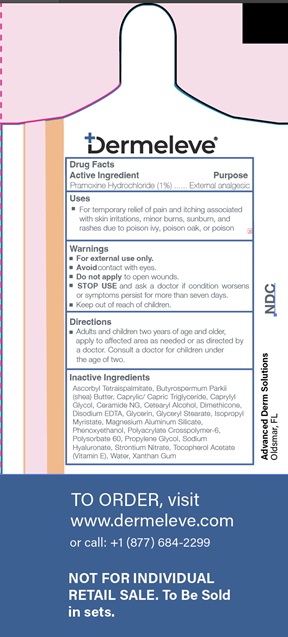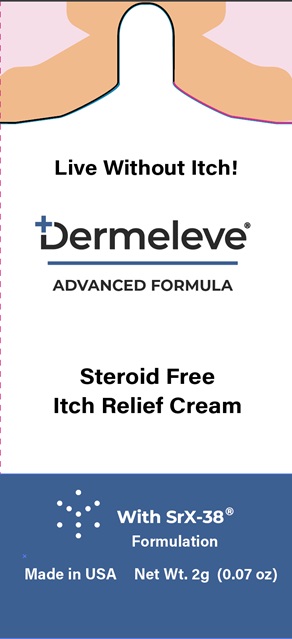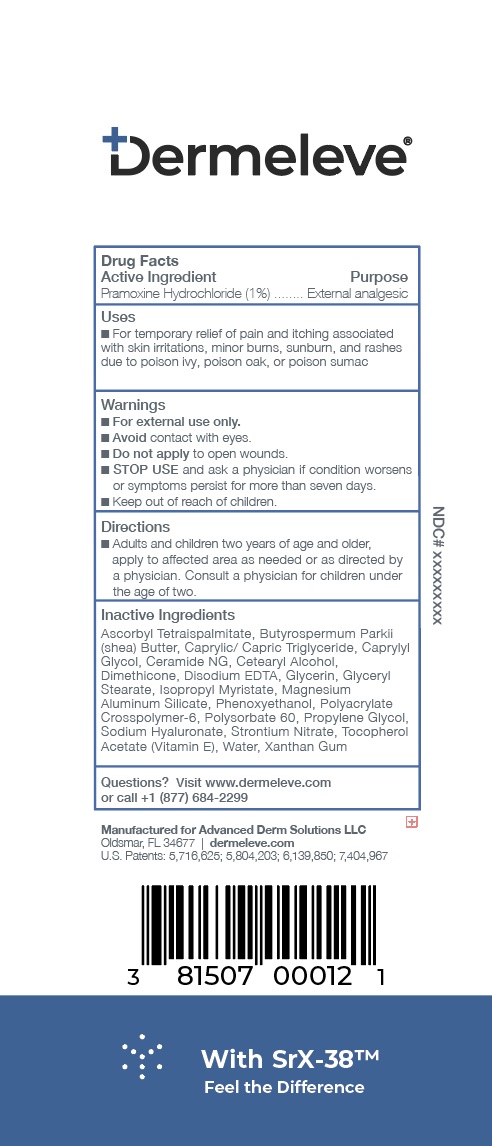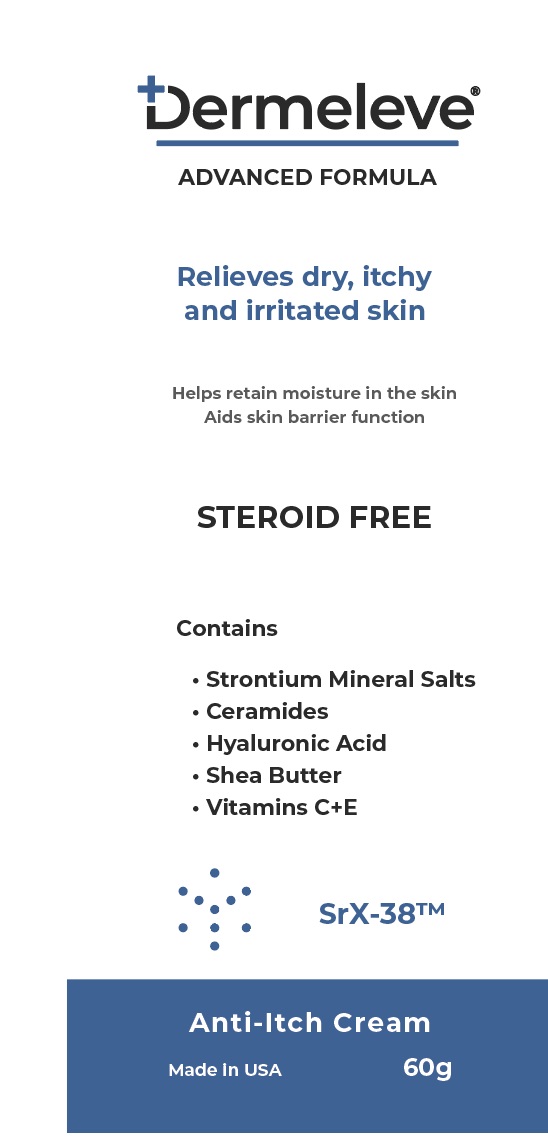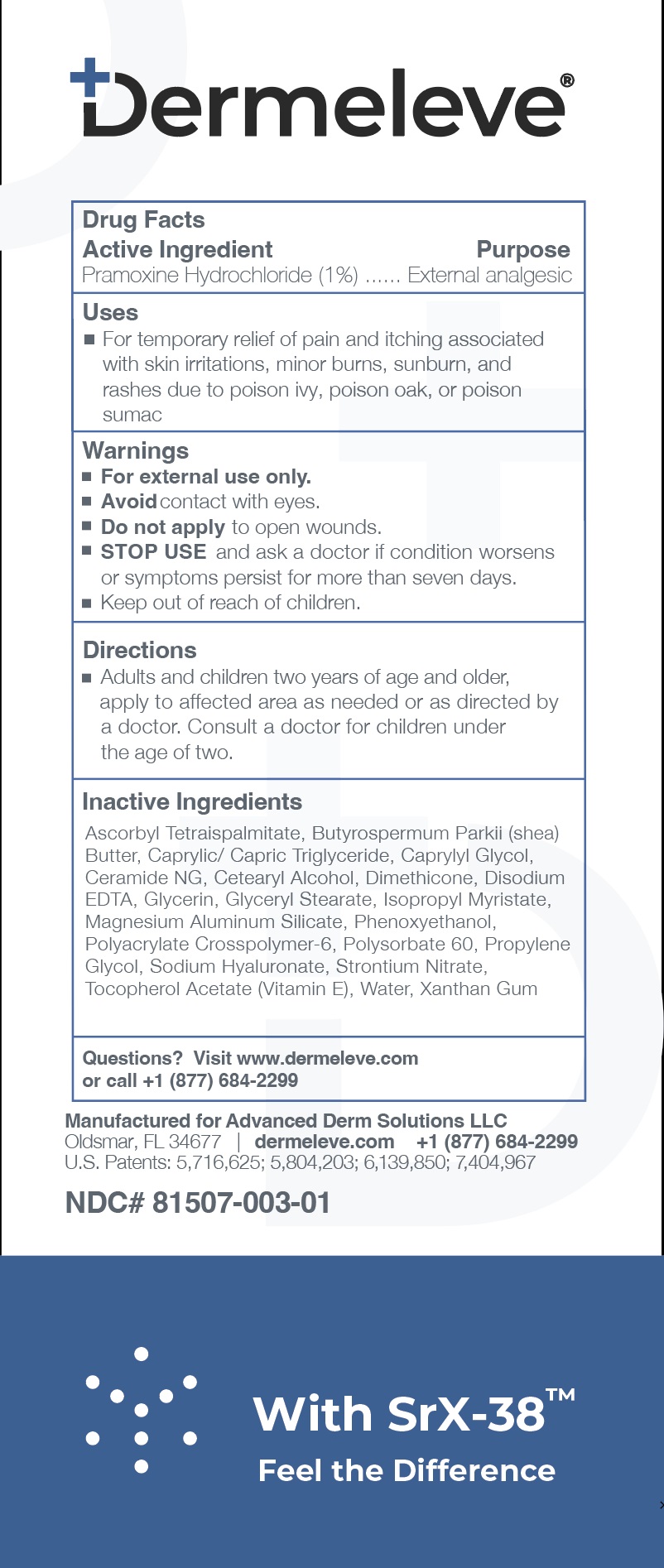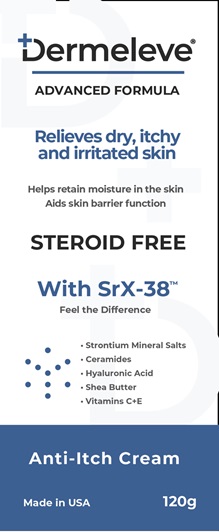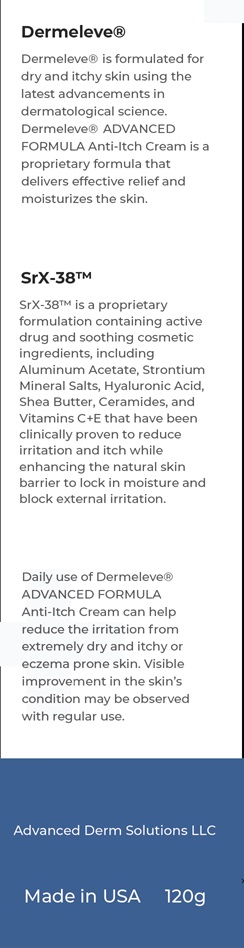 DRUG LABEL: Dermeleve
NDC: 81507-005 | Form: CREAM
Manufacturer: Advanced Derm Solutions LLC
Category: otc | Type: HUMAN OTC DRUG LABEL
Date: 20240816

ACTIVE INGREDIENTS: PRAMOXINE HYDROCHLORIDE 1 g/100 g
INACTIVE INGREDIENTS: ISOPROPYL MYRISTATE; CAPRYLIC/CAPRIC MONO/DI-GLYCERIDES; CETOSTEARYL ALCOHOL; DIMETHICONE 100; POLYACRYLIC ACID (450000 MW); HYALURONIC ACID; PROPYLENE GLYCOL; POLAWAX POLYSORBATE; GLYCERIN; CAPRYLYL GLYCOL; XANTHAN GUM; CERAMIDE NG; WATER O-18; MAGNESIUM ALUMINUM SILICATE TYPE IA; GLYCERYL STEARATE SE; EDETATE DISODIUM; TOCOPHEROL; TETRAHEXYLDECYL ASCORBATE; SHEA BUTTER; PHENOXYETHANOL; STRONTIUM NITRATE

Active Ingredient

Pramoxine Hydrochloride (1%)

Purpose

External analgesic

Uses

For temporary relief of pain and itching associated with skin irritations, minor burns, sunburn, and rashes due to poison ivy, poison oak, or poison sumac

Warnings

- For external use only.
- Avoidcontact with eyes.
- Do not apply to open wounds.
- STOP USE and ask a doctor if condition worsens or symptoms persist for more than seven days.
- Keep out of reach of children.

Directions

Adults and children two years of age and older, apply to affected area as needed or as directed by a doctor.

Consult a doctor for children under the age of two.

Store at 20-25ºC (68-77ºF). Keep carton for full product information

Questions? Visit www.dermeleve.com or call +1 (877)-684-2299

Inactive ingredients

Ascorbyl Tetraispalmitate, Butyrospermum Parkii (shea) Butter, Caprylic/Capric Triglyceride, Caprylyl Glycol, Ceramide NG, Cetearyl Alcohol
Dimethicone, Disodium EDTA, Glycerin, Glyceryl Stearate, Isopropyl Myristate, Magnesium Aluminum Silicate, Phenoxyethanol, Polyacrylate Crosspolymer-6, Polysorbate 60, Propylene Glycol, Sodium Hyaluronate, Strontium Nitrate, Tocopherol Acetate (Vitamin E), Water, Xanthan Gum